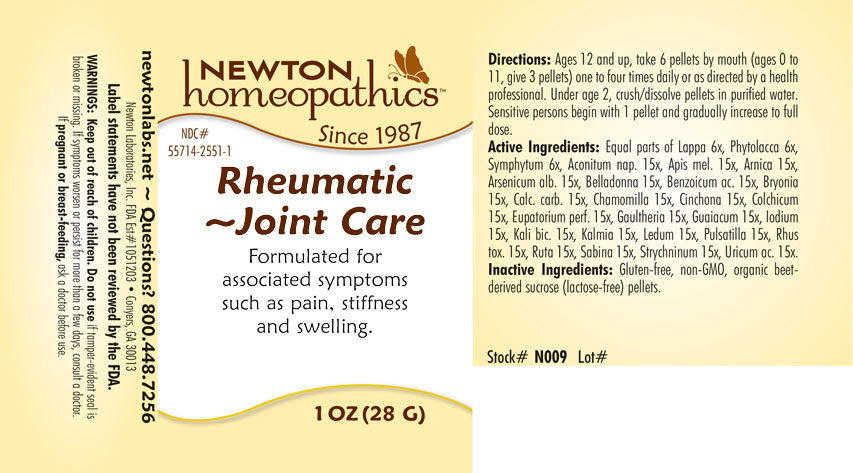 DRUG LABEL: Rheumatic-Joint Care
NDC: 55714-2551 | Form: PELLET
Manufacturer: Newton Laboratories, Inc.
Category: homeopathic | Type: HUMAN OTC DRUG LABEL
Date: 20250210

ACTIVE INGREDIENTS: URIC ACID 15 [hp_X]/1 g; ACONITUM NAPELLUS 15 [hp_X]/1 g; APIS MELLIFERA 15 [hp_X]/1 g; ARNICA MONTANA 15 [hp_X]/1 g; ARSENIC TRIOXIDE 15 [hp_X]/1 g; ATROPA BELLADONNA 15 [hp_X]/1 g; BENZOIC ACID 15 [hp_X]/1 g; BRYONIA ALBA ROOT 15 [hp_X]/1 g; OYSTER SHELL CALCIUM CARBONATE, CRUDE 15 [hp_X]/1 g; MATRICARIA CHAMOMILLA 15 [hp_X]/1 g; CINCHONA OFFICINALIS BARK 15 [hp_X]/1 g; COLCHICUM AUTUMNALE BULB 15 [hp_X]/1 g; EUPATORIUM PERFOLIATUM FLOWERING TOP 15 [hp_X]/1 g; GAULTHERIA PROCUMBENS TOP 15 [hp_X]/1 g; GUAIACUM OFFICINALE RESIN 15 [hp_X]/1 g; IODINE 15 [hp_X]/1 g; POTASSIUM DICHROMATE 15 [hp_X]/1 g; KALMIA LATIFOLIA LEAF 15 [hp_X]/1 g; RHODODENDRON TOMENTOSUM LEAFY TWIG 15 [hp_X]/1 g; ANEMONE PULSATILLA 15 [hp_X]/1 g; TOXICODENDRON PUBESCENS LEAF 15 [hp_X]/1 g; RUTA GRAVEOLENS FLOWERING TOP 15 [hp_X]/1 g; JUNIPERUS SABINA LEAFY TWIG 15 [hp_X]/1 g; STRYCHNINE 15 [hp_X]/1 g; ARCTIUM LAPPA ROOT 6 [hp_X]/1 g; PHYTOLACCA AMERICANA ROOT 6 [hp_X]/1 g; COMFREY ROOT 6 [hp_X]/1 g
INACTIVE INGREDIENTS: SUCROSE

Rheumatic 2551P

INDICATIONS & USAGE SECTION

Formulated for associated symptoms such as pain, stiffness and swelling.

DOSAGE & ADMINISTRATION SECTION

Directions: Ages 12 and up, take 6 pellets by mouth (ages 0 to 11, give 3 pellets) one to four times daily or as directed by a health professional. Under age 2, crush/dissolve pellets in purified water. Sensitive persons begin with 1 pellet and gradually increase to full dose.

OTC - ACTIVE INGREDIENT SECTION

Active Ingredients: Equal parts of Lappa major 6x, Phytolacca decandra 6x, Symphytum officinale 6x, Aconitum napellus 15x, Apis mellifica 15x, Arnica montana 15x, Arsenicum album 15x, Belladonna 15x, Benzoicum acidum 15x, Bryonia 15x, Calcarea carbonica 15x, Chamomilla 15x, Cinchona officinalis 15x, Colchicum autumnale 15x, Eupatorium perfoliatum 15x, Gaultheria procumbens 15x, Guaiacum 15x, Iodium 15x, Kali bichromicum 15x, Kalmia latifolia 15x, Ledum palustre 15x, Pulsatilla 15x, Rhus toxicodendron 15x, Ruta graveolens 15x, Sabina 15x, Strychninum 15x, Uricum acidum 15x.

OTC - PURPOSE SECTION

Formulated for associated symptoms such as pain, stiffness and swelling.

INACTIVE INGREDIENT SECTION

Inactive Ingredients: Gluten-free, non-GMO, organic beet-derived sucrose (lactose-free) pellets.

QUESTIONS SECTION

newtonlabs.net – Questions? 800.448.7256

Newton Laboratories, Inc. FDA Est # 1051203 - Conyers, GA 30013

WARNINGS SECTION

WARNINGS: Keep out of reach of children. Do not use if tamper-evident seal is broken or missing. If symptoms worsen or persist for more than a few days, consult a doctor. If pregnant or breast-feeding, ask a doctor before use.

OTC - PREGNANCY OR BREAST FEEDING SECTION

If pregnant or breast-feeding, ask a doctor before use.

OTC - KEEP OUT OF REACH OF CHILDREN SECTION

Keep out of reach of children.